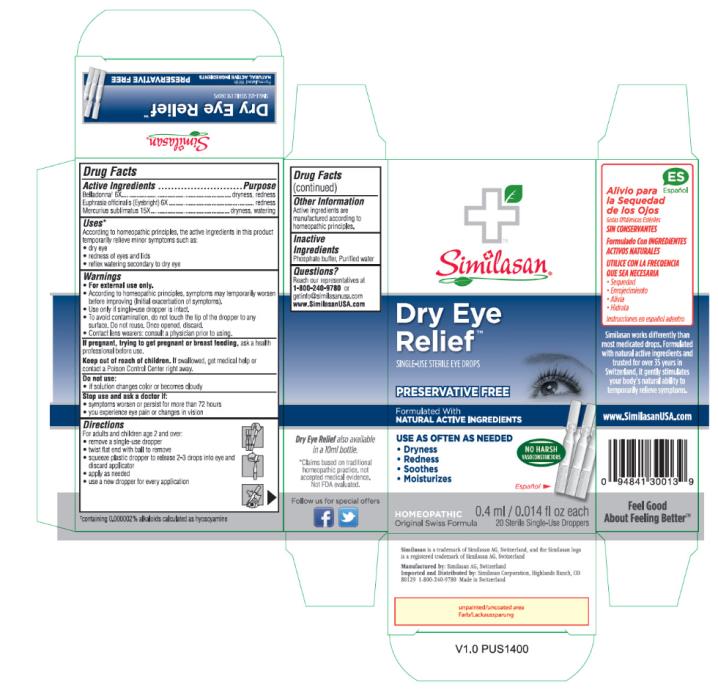 DRUG LABEL: Dry Eye Relief
NDC: 53799-300 | Form: SOLUTION/ DROPS
Manufacturer: Similasan AG
Category: homeopathic | Type: HUMAN OTC DRUG LABEL
Date: 20201007

ACTIVE INGREDIENTS: ATROPA BELLADONNA 6 [hp_X]/0.4 mL; EUPHRASIA STRICTA 6 [hp_X]/0.4 mL; MERCURIC CHLORIDE 15 [hp_X]/0.4 mL
INACTIVE INGREDIENTS: SODIUM PHOSPHATE, MONOBASIC, DIHYDRATE; SODIUM PHOSPHATE, DIBASIC, ANHYDROUS; WATER

Dry Eye Relief Monodose 15x

Drug Facts

Active Ingredients

Belladonna† 6X

Euphrasia officinalis (Eyebright) 6X

Mercurius sublimatus 15X

Purpose

dryness, redness

redness

dryness, watering

Uses*

According to homeopathic principles, the active ingredients in this product temporarily relieve minor symptoms such as:

• dry eye

• redness of eyes and lids

• reflex watering secondary to dry eye

Warnings

• For external use only.

• According to homeopathic principles, symptoms may temporarily worsen before improving (Initial exacerbation of symptoms).

• Use only if single-use dropper is intact.

• To avoid contamination, do not touch the tip of the dropper to any surface. Do not reuse. Once opened, discard.

• Contact lens wearers: consult a physician prior to using.

Keep out of reach of children.

If swallowed, get medical help or contact a Poison Control Center right away.

Do not use:

• if solution changes color or becomes cloudy

Stop use and ask a doctor if:

• symptoms worsen or persist for more than 72 hours

• you experience eye pain or changes in vision

Directions

For adults and children age 2 and over:

• remove a single-use dropper

• twist flat end with ball to remove

• squeeze plastic dropper to release 2-3 drops into eye and discard applicator

• apply as needed

• use a new dropper for every application

Other Information

Active ingredients are manufactured according to homeopathic principles.

Inactive Ingredients

Phosphate buffer, Purified water

Questions?

Reach our representatives at 1-800-240-9780 or getinfo@similasanusa.com

www.SimilasanUSA.com

PRINCIPAL DISPLAY PANEL

Dry Eye
Relief
0.4 ml/0.014 fl oz each